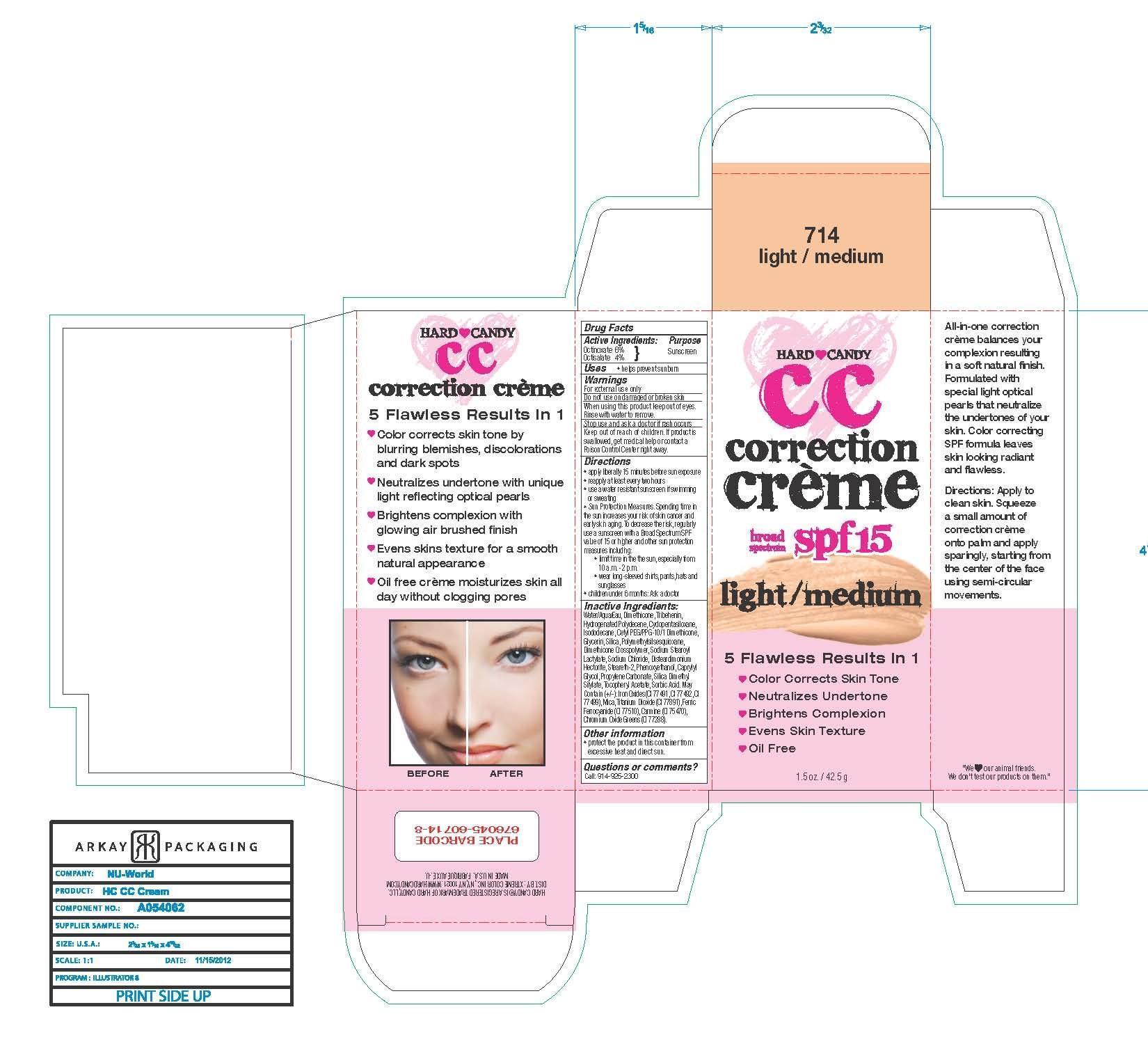 DRUG LABEL: Hard Candy Correction Creme
NDC: 58875-101 | Form: CREAM
Manufacturer: Xtreme Color Inc.
Category: otc | Type: HUMAN OTC DRUG LABEL
Date: 20130827

ACTIVE INGREDIENTS: Octinoxate 2.55 g/42.5 g; OCTISALATE 1.7 g/42.5 g
INACTIVE INGREDIENTS: DIMETHICONE 5.15525 g/42.5 g; HYDROGENATED POLYDECENE (550 MW) 2.55425 g/42.5 g; CETYL PEG/PPG-10/1 DIMETHICONE (HLB 5) 1.27925 g/42.5 g; FERROSOFERRIC OXIDE 1.1333 g/42.5 g; TITANIUM DIOXIDE 0.189 g/42.5 g; FERRIC OXIDE RED 1.1333 g/42.5 g; FERRIC OXIDE YELLOW 1.1333 g/42.5 g; SILICA DIMETHYL SILYLATE 0.0425 g/42.5 g; SILICON DIOXIDE 1.0115 g/42.5 g; POLYMETHYLSILSESQUIOXANE (4.5 MICRONS) 0.85 g/42.5 g; TRIBEHENIN 2.89425 g/42.5 g; CYCLOMETHICONE 5 2.171113 g/42.5 g; DISTEARDIMONIUM HECTORITE 0.255425 g/42.5 g; PROPYLENE CARBONATE 0.127713 g/42.5 g; .ALPHA.-TOCOPHEROL ACETATE 0.0425 g/42.5 g; PHENOXYETHANOL 0.17595 g/42.5 g; SORBIC ACID 0.02125 g/42.5 g; CAPRYLYL GLYCOL 0.1428 g/42.5 g; ISODODECANE 1.70425 g/42.5 g; WATER 13.68625 g/42.5 g; GLYCERIN 1.27925 g/42.5 g; SODIUM CHLORIDE 0.425 g/42.5 g; MICA 0.195 g/42.5 g; CHROMIC OXIDE .006 g/42.5 g; FERRIC FERROCYANIDE .001 g/42.5 g; CARMINIC ACID .003 g/42.5 g; SODIUM STEAROYL LACTYLATE 0.425 g/42.5 g; STEARETH-2 0.2125 g/42.5 g

Hard Candy Correction Creme
Broad Spectrum SPF-15

WARNINGS AND PRECAUTIONS

For external use only.

Do not use on damaged or broken skin.

When using this product keep out of eyes.

Rinse with water to remove.

Stop use and ask a doctor if rash occurs.